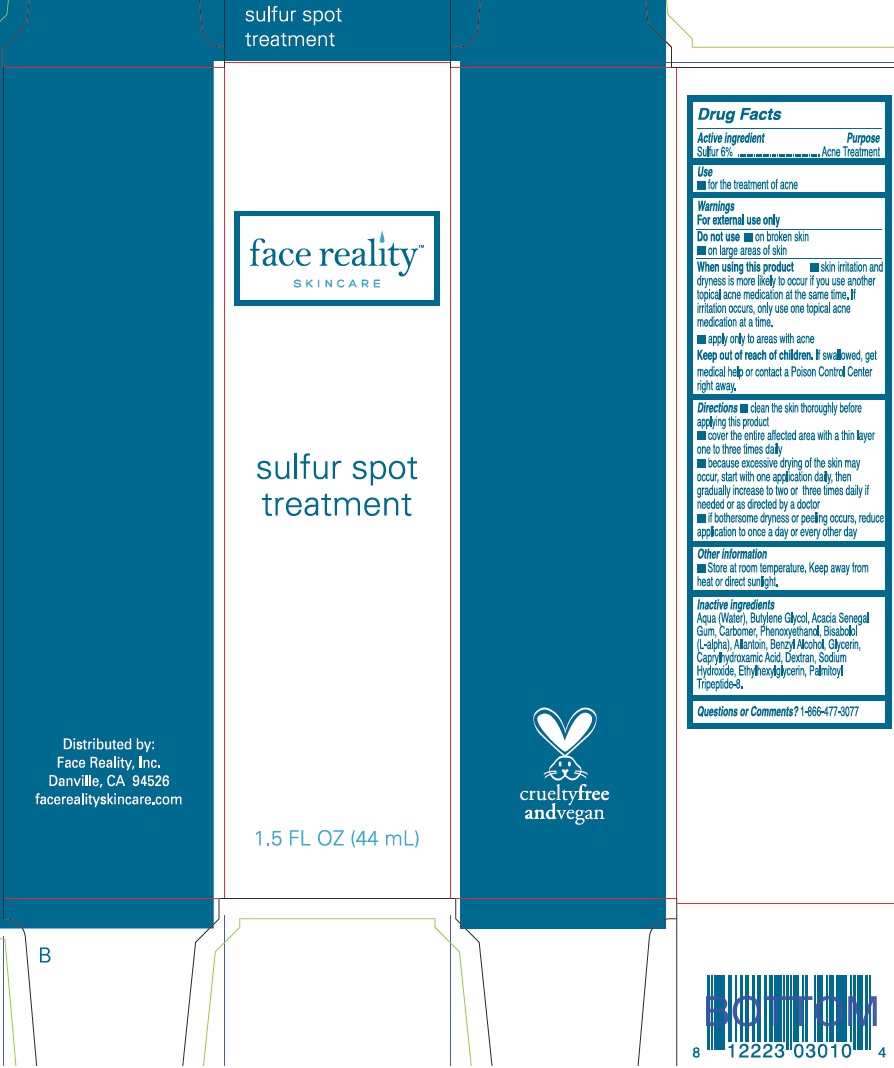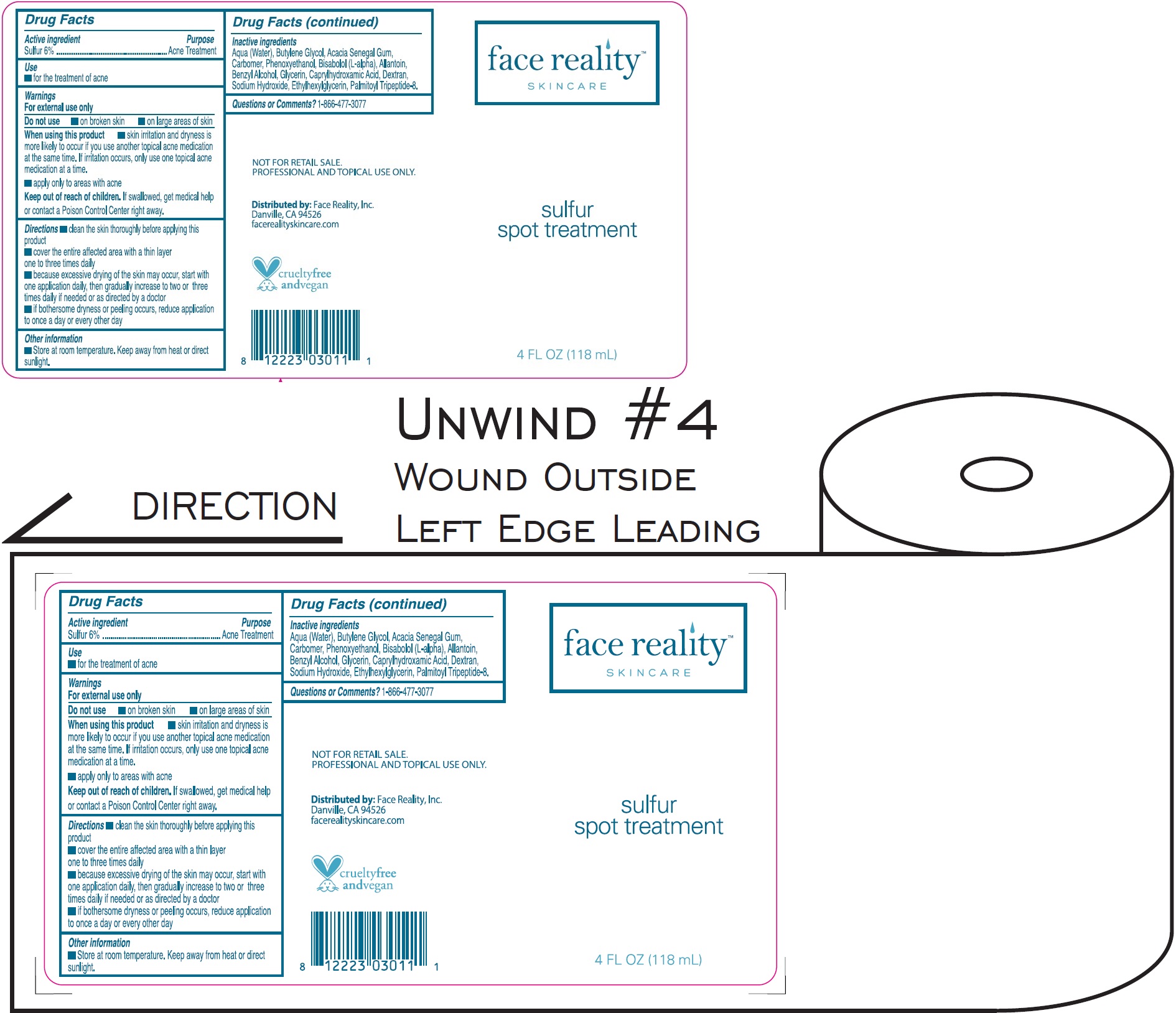 DRUG LABEL: Sulfur Spot Treatment
NDC: 70707-440 | Form: GEL
Manufacturer: Face Reality, Inc
Category: otc | Type: HUMAN OTC DRUG LABEL
Date: 20241209

ACTIVE INGREDIENTS: SULFUR 60 mg/1 mL
INACTIVE INGREDIENTS: BUTYLENE GLYCOL; ACACIA; CARBOMER HOMOPOLYMER, UNSPECIFIED TYPE; PHENOXYETHANOL; WATER; ALLANTOIN; BENZYL ALCOHOL; GLYCERIN; CAPRYLHYDROXAMIC ACID; SODIUM HYDROXIDE; ETHYLHEXYLGLYCERIN; PALMITOYL TRIPEPTIDE-8

Sulfur Spot Treatment

Active ingredient

Sulfur 6%

Purpose

Acne Treatment

Use

for the treatment of acne

Warnings

For external use only

Do not use

- on broken skin
- on large areas of skin

When using this product

- skin irritation and dryness is more likely to occur if you use another topical acne medication at the same time. If irritation occurs, only use one topical acne medication at a time.
- apply only to areas with acne

Keep out of reach of children.

If swallowed, get medical help or contact a Poison Control Center right away.

Directions

- clean the skin thoroughly before applying this product
- cover the entire affected area with a thin layer one to three times daily
- because excessive drying of the skin may occur, start with one application daily, then gradually increase to two or three times daily if needed or as directed by a doctor
- if bothersome dryness or peeling occurs, reduce application to once a day or every other day

Other information

Store at room temperature. Keep away from heat or direct sunlight.

Inactive ingredients

Aqua (Water), Butylene Glycol, Acacia Senegal Gum, Carbomer, Phenoxyethanol, Bisabolol (L-alpha), Allantoin, Benzyl Alcohol, Glycerin, Caprylhydroxamic Acid, Dextran, Sodium Hydroxide, Ethylhexylglycerin, Palmitoyl Tripeptide-8.

Questions or Comments?

1-866-477-3077